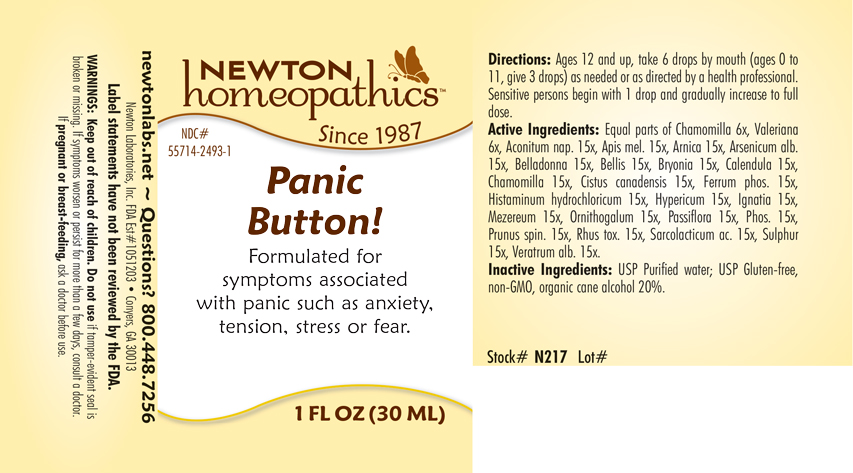 DRUG LABEL: Panic Button
NDC: 55714-2493 | Form: LIQUID
Manufacturer: Newton Laboratories, Inc.
Category: homeopathic | Type: HUMAN OTC DRUG LABEL
Date: 20250207

ACTIVE INGREDIENTS: ACONITUM NAPELLUS 15 [hp_X]/1 mL; APIS MELLIFERA 15 [hp_X]/1 mL; ARNICA MONTANA 15 [hp_X]/1 mL; ARSENIC TRIOXIDE 15 [hp_X]/1 mL; ATROPA BELLADONNA 15 [hp_X]/1 mL; BELLIS PERENNIS 15 [hp_X]/1 mL; BRYONIA ALBA ROOT 15 [hp_X]/1 mL; CALENDULA OFFICINALIS FLOWERING TOP 15 [hp_X]/1 mL; MATRICARIA CHAMOMILLA 15 [hp_X]/1 mL; HELIANTHEMUM CANADENSE 15 [hp_X]/1 mL; STRYCHNOS IGNATII SEED 15 [hp_X]/1 mL; FERROSOFERRIC PHOSPHATE 15 [hp_X]/1 mL; HISTAMINE DIHYDROCHLORIDE 15 [hp_X]/1 mL; HYPERICUM PERFORATUM 15 [hp_X]/1 mL; DAPHNE MEZEREUM BARK 15 [hp_X]/1 mL; ORNITHOGALUM UMBELLATUM 15 [hp_X]/1 mL; PASSIFLORA INCARNATA FLOWERING TOP 15 [hp_X]/1 mL; PHOSPHORUS 15 [hp_X]/1 mL; PRUNUS SPINOSA FLOWER BUD 15 [hp_X]/1 mL; TOXICODENDRON PUBESCENS LEAF 15 [hp_X]/1 mL; LACTIC ACID, L- 15 [hp_X]/1 mL; SULFUR 15 [hp_X]/1 mL; VERATRUM ALBUM ROOT 15 [hp_X]/1 mL; VALERIAN 6 [hp_X]/1 mL
INACTIVE INGREDIENTS: ALCOHOL; WATER

Panic 2493L

INDICATIONS & USAGE SECTION

Formulated for symptoms associated with panic such as anxiety, tension, stress or fear.

DOSAGE & ADMINISTRATION SECTION

Directions: Ages 12 and up, take 6 drops by mouth (ages 0 to 11, give 3 drops) as needed or as directed by a health professional. Sensitive persons begin with 1 drop and gradually increase to full dose.

OTC - ACTIVE INGREDIENT SECTION

Equal parts of Chamomilla 6x, Valeriana officinalis 6x, Aconitum napellus 15x, Apis mellifica 15x, Arnica montana 15x, Arsenicum album 15x, Belladonna 15x, Bellis perennis 15x, Bryonia 15x, Calendula officinalis 15x, Chamomilla 15x, Cistus canadensis 15x, Ferrum phosphoricum 15x, Histaminum hydrochloricum 15x, Hypericum perforatum 15x, Ignatia amara 15x, Mezereum 15x, Ornithogalum umbellatum 15x, Passiflora incarnata 15x, Phosphorus 15x, Prunus spinosa 15x, Rhus toxicodendron 15x, Sarcolacticum acidum 15x, Sulphur 15x, Veratrum album 15x.

OTC - PURPOSE SECTION

Formulated for symptoms associated with panic such as anxiety, tension, stress or fear.

INACTIVE INGREDIENT SECTION

Inactive Ingredients: USP Purified Water; USP Gluten-free, non-GMO, organic cane alcohol 20%.

QUESTIONS SECTION

newtonlabs.net – Questions? 800.448.7256

Newton Laboratories, Inc. FDA Est # 1051203 - Conyers, GA 30013

WARNINGS SECTION

WARNINGS: Keep out of reach of children. Do not use if tamper-evident seal is broken or missing. If symptoms worsen or persist for more than a few days, consult a doctor. If pregnant or breast-feeding, ask a doctor before use.

OTC - PREGNANCY OR BREAST FEEDING SECTION

If pregnant or breast-feeding, ask a doctor before use.

OTC - KEEP OUT OF REACH OF CHILDREN SECTION

Keep out of reach of children.